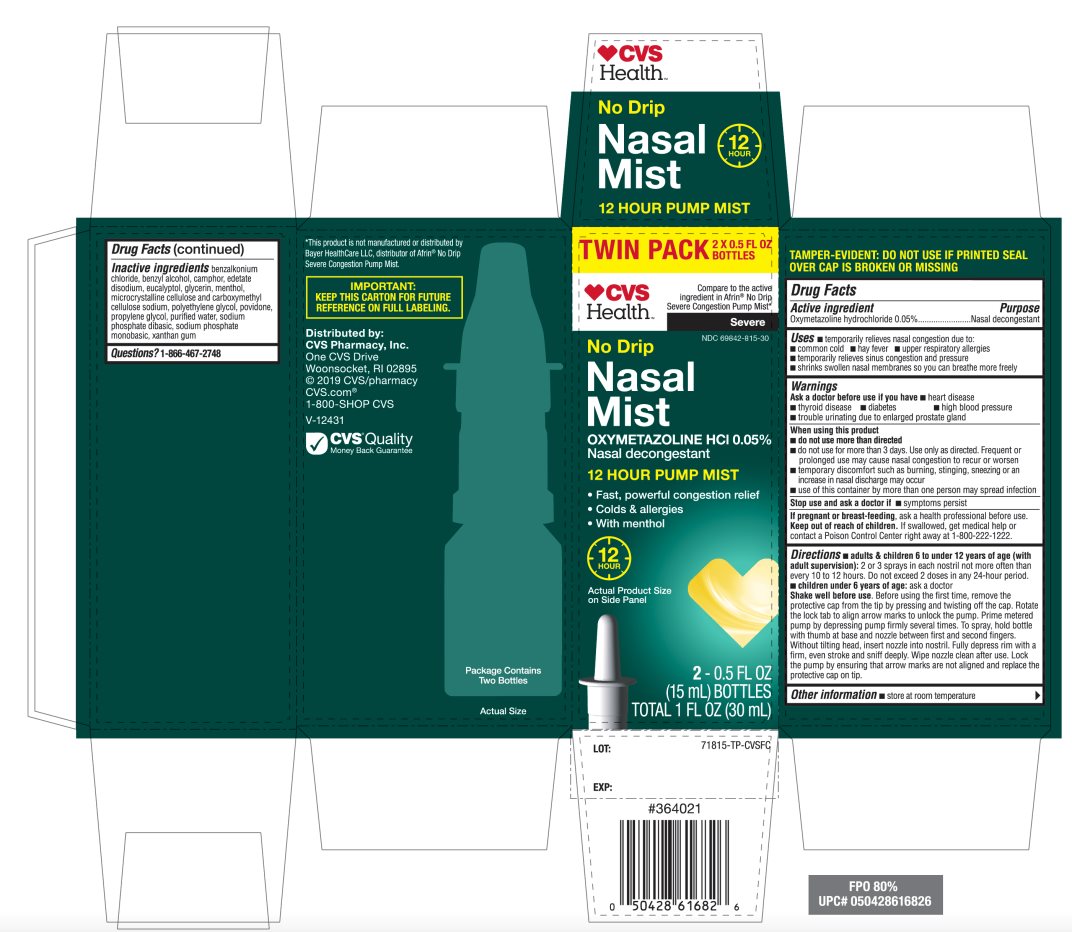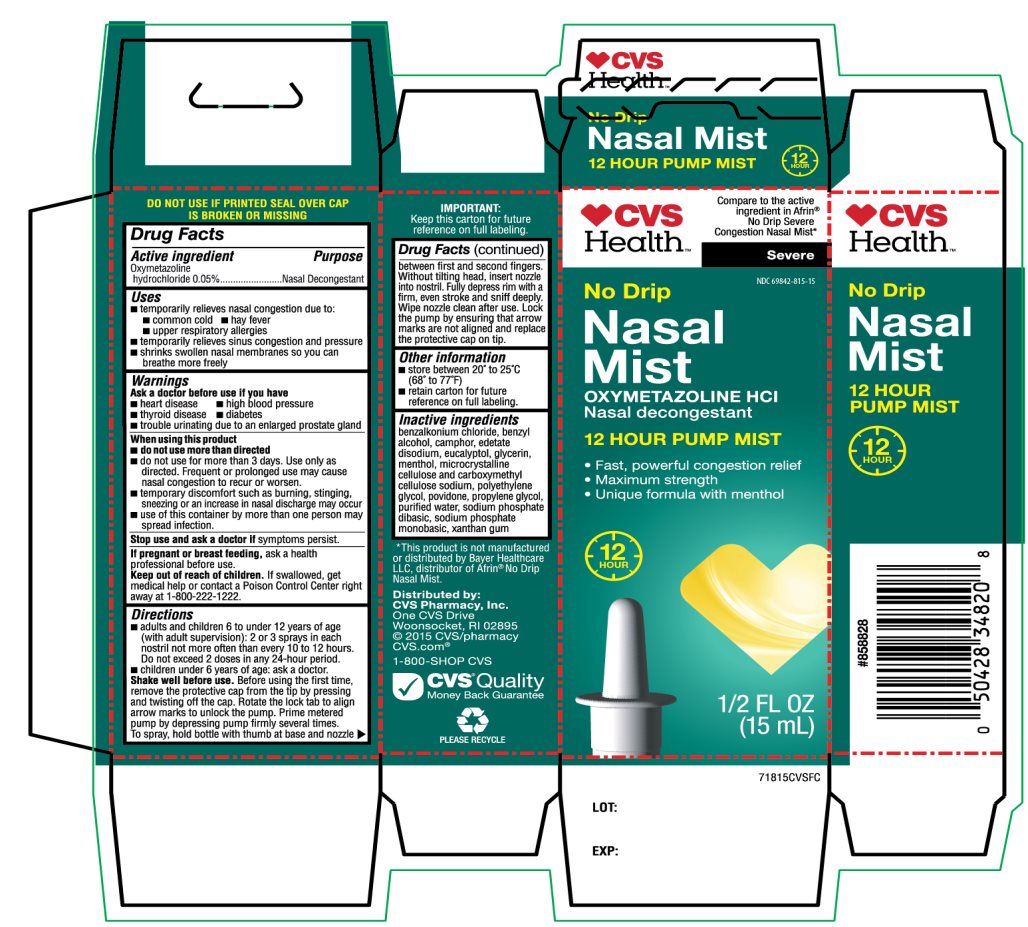 DRUG LABEL: CVS Health

NDC: 69842-815 | Form: SPRAY
Manufacturer: CVS PHARMACY,INC.
Category: otc | Type: HUMAN OTC DRUG LABEL
Date: 20251209

ACTIVE INGREDIENTS: OXYMETAZOLINE HYDROCHLORIDE 0.05 g/100 mL
INACTIVE INGREDIENTS: BENZALKONIUM CHLORIDE; BENZYL ALCOHOL; CAMPHOR (NATURAL); EDETATE DISODIUM; EUCALYPTOL; GLYCERIN; MENTHOL, UNSPECIFIED FORM; MICROCRYSTALLINE CELLULOSE; CARBOXYMETHYLCELLULOSE SODIUM, UNSPECIFIED; POLYETHYLENE GLYCOL, UNSPECIFIED; POVIDONE, UNSPECIFIED; PROPYLENE GLYCOL; WATER; SODIUM PHOSPHATE, DIBASIC, UNSPECIFIED FORM; SODIUM PHOSPHATE, MONOBASIC, UNSPECIFIED FORM; XANTHAN GUM

CVS Health No Drip Nasal Mist Drug Facts

Active ingredient

Oxymetazoline hydrochloride 0.05%

Purpose

Nasal Decongestant

Uses

- temporarily relieves nasal congestion due to:
- common cold
- hay fever
- upper respiratory allergies
- temporarily relieves sinus congestion and pressure
- shrinks swollen nasal membranes so you can breathe more freely

Ask a doctor before use if you have

- heart disease
- high blood pressure
- thyroid disease
- diabetes
- trouble urinating due to an enlarged prostate gland

When using this product

- do not use more than directed
- do not use for more than 3 days. Use only as directed. Frequent or prolonged use may cause nasal congestion to recur or worsen.
- temporary discomfort such as burning, stinging, sneezing or an increase in nasal discharge may occur
- use of this container by more than one person may spread infection

Stop use and ask a doctor if

symptoms persist

If pregnant or breast-feeding,

ask a health professional before use.

Keep out of reach of children.

If swallowed, get medical help or contact a Poison Control Center right away at (1-800-222-1222).

Directions

- adults and children 6 to under 12 years of age (with adult supervision):2 or 3 sprays in each nostril not more often than every 10 to 12 hours. Do not exceed 2 doses in any 24-hour period.
- children under 6 years of age:ask a doctor

Shake well before use.Before using the first time, remove the protective cap from the tip by pressing and twisting off the cap. Rotate the lock tab to align arrow marks to unlock the pump. Prime metered pump by depressing pump firmly several times. To spray, hold bottle with thumb at base and nozzle between first and second fingers. Without tilting head, insert nozzle into nostril. Fully depress rim with a firm, even stroke and sniff deeply. Wipe nozzle clean after use. Lock the pump by ensuring that arrow marks are not aligned and replace the proactive cap on tip.

Other information

- store between 20 to 25°C (68 to 77°F)
- Retain carton for future reference on full labeling.

TAMPER-EVIDENT: DO NOT USE IF PRINTED SEAL OVER CAP IS BROKEN OR MISSING

Inactive ingredients

benzalkonium chloride, benzyl alcohol, camphor, edetate disodium, eucalyptol, glycerin, menthol, microcrystalline cellulose and carboxymethylcellulose sodium, polyethylene glycol, povidone, propylene glycol, purified water, sodium phosphate dibasic, sodium phosphate monobasic, xanthan gum.

Package/Label Principal Display Panel

CVS Health™

Compare to active ingredient in Afrin® No Drip Severe Congestion Nasal Mist*

Severe

No-Drip Nasal Mist

OXYMETAZOLINE HCL

Nasal Decongestant

12 HOUR PUMP MIST

- Fast and Powerful Congestion Relief
- Maximum Strength
- Unique formula with menthol

12 HOURS

Distributed by:

CVS Pharmacy, Inc.

One CVS Drive

Woonsocket, RI 02895

© 2015 CVS/pharmacy

CVS.com®

1-800-SHOP CVS

CVS®Quality

Money Back Guarantee

IMPORTANT: Keep this carton for future reference on full labeling.

*This product is not manufactured or distributed by Bayer Healthcare LLC, distributor of Afrin®No Drip Nasal Mist.

Package Label 15 mL